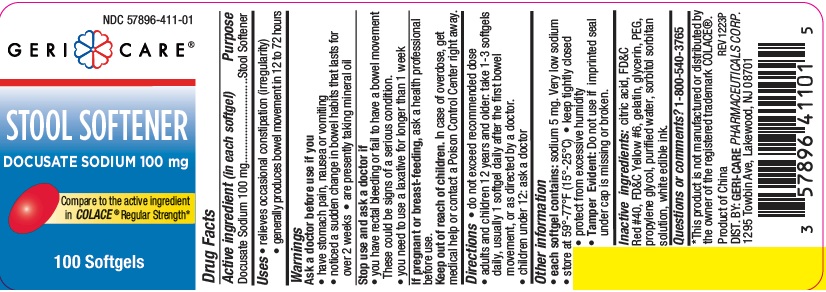 DRUG LABEL: Stool Softener
NDC: 57896-411 | Form: CAPSULE, LIQUID FILLED
Manufacturer: Geri-Care Pharmaceutical Corp
Category: otc | Type: HUMAN OTC DRUG LABEL
Date: 20251204

ACTIVE INGREDIENTS: DOCUSATE SODIUM 100 mg/1 1
INACTIVE INGREDIENTS: FD&C RED NO. 40; GELATIN; GLYCERIN; POLYETHYLENE GLYCOL, UNSPECIFIED; SORBITOL; WATER; FD&C YELLOW NO. 6; PROPYLENE GLYCOL; ANHYDROUS CITRIC ACID; SORBITAN

gc 401

Active ingredient (in each softgel)

Docusate Sodium 100 mg

Purpose

Stool Softener

Uses

- relieves occasional constipation (irregularity)

- generally produces bowel movement in 12 to 72 hours

Warnings

Ask a doctor before use if you

• have stomach pain, nausea or vomiting

• noticed a sudden change in bowel habits that lasts for over a period of 2 weeks

• are presently taking mineral oil

Stop use and ask a doctor if

• you have rectal bleeding or fail to have a bowel movement.

These could be signs of a serious condition.

• you need to use a laxative for longer than 1 week

If pregnant or breast-feeding, ask a health professional before use.

Keep out of reach of children. In case of overdose, get medical help or contact a Poison Control Center right away.

Directions

- do not exceed recommended dose
- adults and children 12 years and older: take 1-3 softgels daily, usually 1 softgel daily after the first bowel movement, or as directed by a doctor.
- children under 12: ask a doctor

Other information

• each softgel contains: sodium 5 mg. Very low sodium
• store at 59°-77°F (15°-25°C)
• keep tightly closed
• Tamper Evident: Do not use if imprinted seal
under cap is missing or broken.

Inactive ingredients

citric acid, FD&C Red #40, FD&C Yellow #6, gelatin, glycerin, PEG, propylene glycol, purified water, sorbitol sorbitan
solution, white edible ink.

Questions or comments?

1-800-540-3765